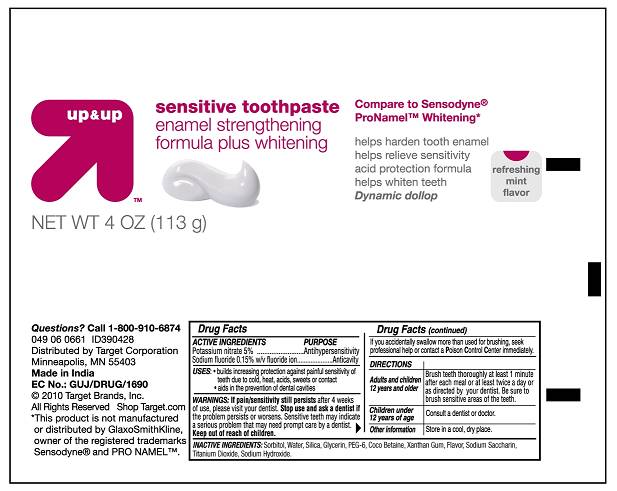 DRUG LABEL: Up and UP Sensitive Toothpaste Enamel Strengthening formula plus whitening
NDC: 67659-081 | Form: PASTE
Manufacturer: Team Technologies, Inc
Category: otc | Type: HUMAN OTC DRUG LABEL
Date: 20100825

ACTIVE INGREDIENTS: POTASSIUM NITRATE 5 mg/1 g; SODIUM FLUORIDE 1.5 mg/1 g
INACTIVE INGREDIENTS: SORBITOL; WATER; SILICON DIOXIDE; GLYCERIN; POLYETHYLENE GLYCOL 300; COCAMIDOPROPYL BETAINE; XANTHAN GUM; SACCHARIN SODIUM; TITANIUM DIOXIDE; SODIUM HYDROXIDE

UP & Up Sensitive Toothpaste Enamel Strengthening formula plus whitening

Active Ingredients

Potassium nitrate 5%................................Antihypersensitivity
Sodium Fluoride 0.15% w/v fluoride ion ......Anticavity

USES

- builds increasing protection against painful sensitivity of teeth due to cold, heat, acids, sweets or contact
- Aids in the prevention of dental cavities

WARNINGS

If pain/ sensitivity still persists after 4 weeks of use, please visit your dentist. Stop use and ask a dentist if the problem persists or worsens. Sensitive teeth may indicate a serious problem that may need prompt care by a dentist. Keep out of reach of children. If you accidentally swallow more than used for brushing, seek professional help or contact a Poison Control Center immediately.

Directions

Adults and children 12 years and older Brush teeth thoroughly at least 1 minute after each meal or at least twice a day or as directed by your dentist. Be sure to brush sensitive areas of the teeth.
Children under 12 years of age Consult a dentist or doctor
Other information Store in a cool, dry place.

Inactive ingredients:

Sorbitol, Water, Silica, Glycerin, PEG-6, COCAMIDOPROPYL BETAINE, Xanthan Gum, Flavor, Sodium Saccharin, Titanium Dioxide, Sodium Hydroxide.

PURPOSE

Antihypersensitivity, Anticavity

KEEP OUT OF REACH OF CHILDREN